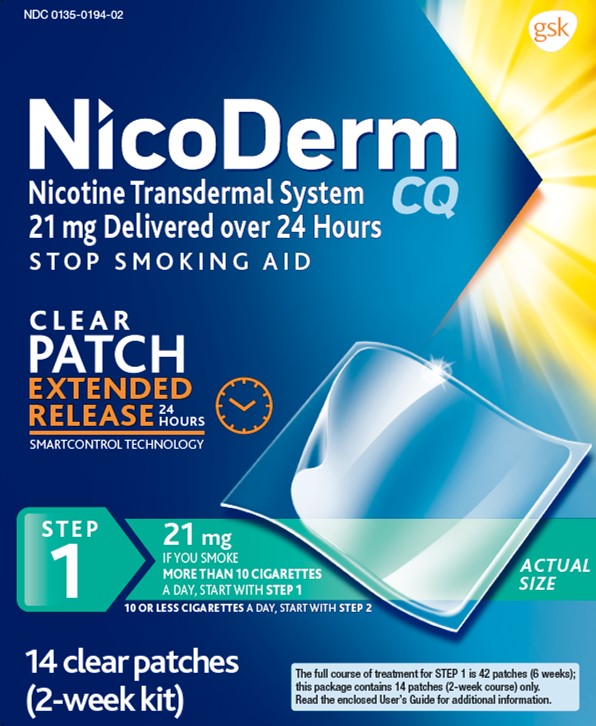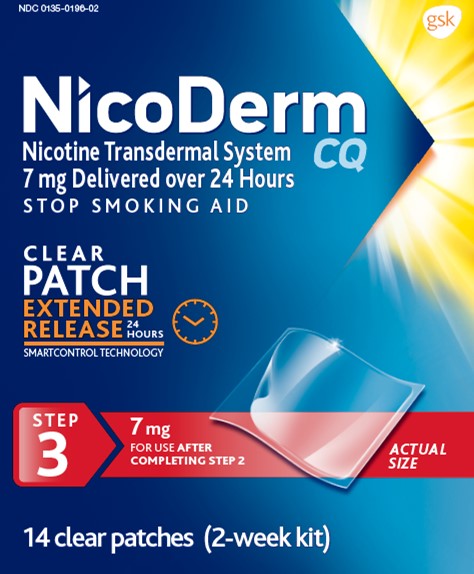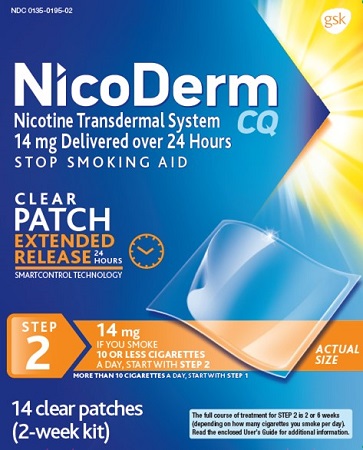 DRUG LABEL: NICODERM

NDC: 0135-0194 | Form: PATCH, EXTENDED RELEASE
Manufacturer: Haleon US Holdings LLC
Category: otc | Type: HUMAN OTC DRUG LABEL
Date: 20250714

ACTIVE INGREDIENTS: NICOTINE 21 mg/24 h
INACTIVE INGREDIENTS: ETHYLENE-VINYL ACETATE COPOLYMER (40% VINYL ACETATE); HIGH DENSITY POLYETHYLENE

Drug Facts

Active ingredient (in each patch)

Nicotine, 21 mg delivered over 24 hours

Active ingredient (in each patch)

Nicotine, 14 mg delivered over 24 hours

Active ingredient (in each patch)

Nicotine, 7 mg delivered over 24 hours

Purpose

Stop smoking aid

Use

reduces withdrawal symptoms, including nicotine craving, associated with quitting smoking

Warnings

If you are pregnant or breast-feeding, only use this medicine on the advice of your health care provider.

Smoking can seriously harm your child. Try to stop smoking without using any nicotine replacement medicine. This medicine is believed to be safer than smoking. However, the risks to your child from this medicine are not fully known.

Ask a doctor before use if you have

- heart disease, recent heart attack, or irregular heartbeat. Nicotine can increase your heart rate.
- high blood pressure not controlled with medication. Nicotine can increase your blood pressure.
- an allergy to adhesive tape or have skin problems because you are more likely to get rashes
- stomach ulcers or diabetes
- history of seizures

Ask a doctor or pharmacist before use if you are

- using a non-nicotine stop smoking drug
- taking a prescription medicine for depression or asthma. Your prescription dose may need to be adjusted.

When using this product

- if you have vivid dreams or other sleep disturbances remove this patch at bedtime

Stop use and ask a doctor if

- skin redness caused by the patch does not go away after four days, or if your skin swells, or you get a rash
- irregular heartbeat or palpitations occur
- you get symptoms of nicotine overdose such as nausea, vomiting, dizziness, weakness and rapid heartbeat
- you have symptoms of an allergic reaction (such as difficulty breathing or rash)

Keep out of reach of children and pets.

Used patches have enough nicotine to poison children and pets. If swallowed, get medical help or contact a Poison Control Center right away. Dispose of the used patches by folding sticky ends together. Replace in pouch and discard.

Directions

- if you are under 18 years of age, ask a doctor before use
- before using this product, read the enclosed User's Guide for complete directions and other information
- begin using the patch on your quit day
- if you smoke more than 10 cigarettes per day,use according to the following 10-week schedule:

STEP 1 | STEP 2 | STEP 3
Use one 21 mg patch/day | Use one 14 mg patch/day | Use one 7 mg patch/day
Weeks 1-6 | Weeks 7-8 | Weeks 9-10

- if you smoke 10 or less cigarettes per day,do not use STEP 1 (21 mg).Start with STEP 2 (14 mg)for 6 weeks, then STEP 3 (7 mg)for 2 weeks and then stop.
- steps 2 and 3 allow you to gradually reduce your level of nicotine. Completing the full program will increase your chances of quitting successfully.
- apply one new patch every 24 hours on skin that is dry, clean and hairless. Save pouch for disposing of the patch after use.
- remove backing from patch and immediately press onto skin. Hold for 10 seconds.
- wash hands after applying or removing patch. Throw away the patch by folding sticky ends together. Replace in its pouch and discard. See enclosed User's Guide for safety and handling.
- you may wear the patch for 16 or 24 hours
- if you crave cigarettes when you wake up, wear the patch for 24 hours
- if you have vivid dreams or other sleep disturbances, you may remove the patch at bedtime and apply a new one in the morning
- the used patch should be removed and a new one applied to a different skin site at the same time each day
- do not wear more than one patch at a time
- do not cut patch in half or into smaller pieces
- do not leave patch on for more than 24 hours because it may irritate your skin and loses strength after 24 hours
- it is important to complete treatment. If you feel you need to use the patch for a longer period to keep from smoking, talk to your health care provider.

Other information

- store at 20-25°C (68-77°F)

Inactive ingredients

ethylene vinyl acetate-copolymer, polyisobutylene and high density polyethylene between clear polyester backings

Questions or comments?

call toll-free 1-800-834-5895

Additional Information (Step 1)

Read carton and enclosed User’s Guide before using this product. Keep this carton and User’s Guide. They contain important information.

Includes User’s Guide with MyQuit Program Enrollment Offer.

What is the NicoDerm CQPatch and How is it Used?
NicoDerm CQis a small, nicotine-containing patch. When you put on a NicoDerm CQpatch, nicotine passes through the skin and into your body. NicoDerm CQis very thin and uses special material to control how fast nicotine passes through the skin. Unlike the sudden jolts of nicotine delivered by cigarettes, the amount of nicotine you receive remains relatively smooth throughout the 16 or 24 hour period you wear the NicoDerm CQpatch. This helps to reduce cravings you may have for nicotine.

READ THE LABEL
Nicotine Transdermal System
STOP SMOKING AID
STEP 1
14 clear patches (2-week kit)

- Not for sale to those under 18 years of age.
- Proof of age required.
- Not for sale in vending machines or from any source where proof of age cannot be verified.

Trademarks are owned by or licensed to the GSK group of companies.

For more information and for a FREE individualized stop smoking program, please visit www.nicodermcq.comor see inside for more details.

U.S. Patent No. 7,622,136

8,075,911

TO INCREASE YOUR SUCCESS IN QUITTING:

1. You must be motivated to quit.

2. Complete the full treatment program, applying a new patch every day.

3. Use with a support program as described in the enclosed User's Guide.

For your family's protection, NicoDerm CQpatches are supplied in child resistant pouches. Do not use if individual pouch is open or torn.

NicoDerm CQ is a three step program. You start with the highest level of medicine and

gradually step down your dose. If you smoke 10 or less cigarettes per day, start with Step 2.

Made in Ireland

©2022 GSK group of companies or its licensor.

200697

Additional Information (Step 2)

Read carton and enclosed User’s Guide before using this product. Keep this carton and User’s Guide. They contain important information.

Includes User’s Guide with MyQuit Program Enrollment Offer.

What is the NicoDerm CQPatch and How is it Used?
NicoDerm CQis a small, nicotine-containing patch. When you put on a NicoDerm CQpatch, nicotine passes through the skin and into your body. NicoDerm CQis very thin and uses special material to control how fast nicotine passes through the skin. Unlike the sudden jolts of nicotine delivered by cigarettes, the amount of nicotine you receive remains relatively smooth throughout the 16 or 24 hour period you wear the NicoDerm CQpatch. This helps to reduce cravings you may have for nicotine.

READ THE LABEL
Nicotine Transdermal System
STOP SMOKING AID
STEP 2
14 clear patches (2-week kit)

- Not for sale to those under 18 years of age.
- Proof of age required.
- Not for sale in vending machines or from any source where proof of age cannot be verified.

Trademarks are owned by or licensed to the GSK group of companies.

For more information and for a FREE individualized stop smoking program, please visit www.nicodermcq.comor see inside for more details.

U.S. Patent No. 7,622,136

8,075,911

TO INCREASE YOUR SUCCESS IN QUITTING:

1. You must be motivated to quit.

2. Complete the full treatment program, applying a new patch every day.

3. Use with a support program as described in the enclosed User's Guide.

For your family's protection, NicoDerm CQpatches are supplied in child resistant pouches. Do not use if individual pouch is open or torn.

NicoDerm CQ is a three step program. You start with the highest level of medicine and

gradually step down your dose. If you smoke 10 or less cigarettes per day, start with Step 2.

Made in Ireland

©2022 GSK group of companies or its licensor.

201227

Additional Information (Step 3)

Read carton and enclosed User’s Guide before using this product. Keep this carton and User’s Guide. They contain important information.

Includes User’s Guide with MyQuit Program Enrollment Offer.

What is the NicoDerm CQ Patch and How is it Used?

NicoDerm CQis a small, nicotine-containing patch. When you put on a NicoDerm CQpatch, nicotine passes through the skin and into your body. NicoDerm CQis very thin and uses special material to control how fast nicotine passes through the skin. Unlike the sudden jolts of nicotine delivered by cigarettes, the amount of nicotine you receive remains relatively smooth throughout the 16 or 24 hour period you wear the NicoDerm CQpatch. This helps to reduce cravings you may have for nicotine.

READ THE LABEL
Nicotine Transdermal System
STOP SMOKING AID
STEP 3
14 clear patches (2-week kit)

- Not for sale to those under 18 years of age.
- Proof of age required.
- Not for sale in vending machines or from any source where proof of age cannot be verified.

Trademarks are owned by or licensed to the GSK group of companies.

For more information and for a FREE individualized stop smoking program, please visit www.nicodermcq.comor see inside for more details.

U.S. Patent No. 7,622,136

8,075,911

TO INCREASE YOUR SUCCESS IN QUITTING:

1. You must be motivated to quit.

2. Complete the full treatment program, applying a new patch every day.

3. Use with a support program as described in the enclosed User's Guide.

For your family's protection, NicoDerm CQpatches are supplied in child resistant pouches. Do not use if individual pouch is open or torn.

NicoDerm CQ is a three step program. You start with the highest level of medicine and

gradually step down your dose. If you smoke 10 or less cigarettes per day, start with Step 2.

Made in Ireland

©2022 GSK group of companies or its licensor.

201228

Principal Display Panel

NDC 0135-0194-02

NicoDerm CQ

Nicotine Transdermal System 21 mg Delivered over 24 Hours

STOP SMOKING AID

CLEAR PATCH

EXTENDED RELEASE24 HOURS

SMARTCONTROL TECHNOLOGY

STEP 1

21 mg

IF YOU SMOKE MORE THAN 10 CIGARETTESA DAY, START WITH STEP 1

10 OR LESS CIGARETTESA DAY, START WITH STEP 2

ACTUAL SIZE

14 clear patches(2-week kit)

The full course of treatment for STEP 1 is 42 patches (6 weeks); this package contains 14 patches (2-week course) only.

Read the enclosed User’s Guide for additional information.

Principal Display Panel

NDC 0135-0195-02

NicoDerm CQ

Nicotine Transdermal System 14 mg Delivered over 24 Hours

STOP SMOKING AID

CLEAR PATCH

EXTENDED RELEASE24 HOURS

SMARTCONTROL TECHNOLOGY

STEP 2

14 mg

IF YOU SMOKE 10 OR LESS CIGARETTESA DAY, START WITH STEP 2

MORE THAN 10 CIGARETTESA DAY, START WITH STEP 1

ACTUAL SIZE

14 clear patches(2-week kit)

The full course of treatment for STEP 2 is 2 or 6 weeks (depending on how many cigarettes you smoke per day).
Read the enclosed User’s Guide for additional information.

Principal Display Panel

NDC 0135-0196-02

NicoDerm CQ

Nicotine Transdermal System 7 mg Delivered over 24 Hours

STOP SMOKING AID

CLEAR PATCH

EXTENDED RELEASE24 HOURS

SMARTCONTROL TECHNOLOGY

STEP 3

7 mg

FOR USE AFTER COMPLETING STEP 2

ACTUAL SIZE

14 clear patches(2-week kit)